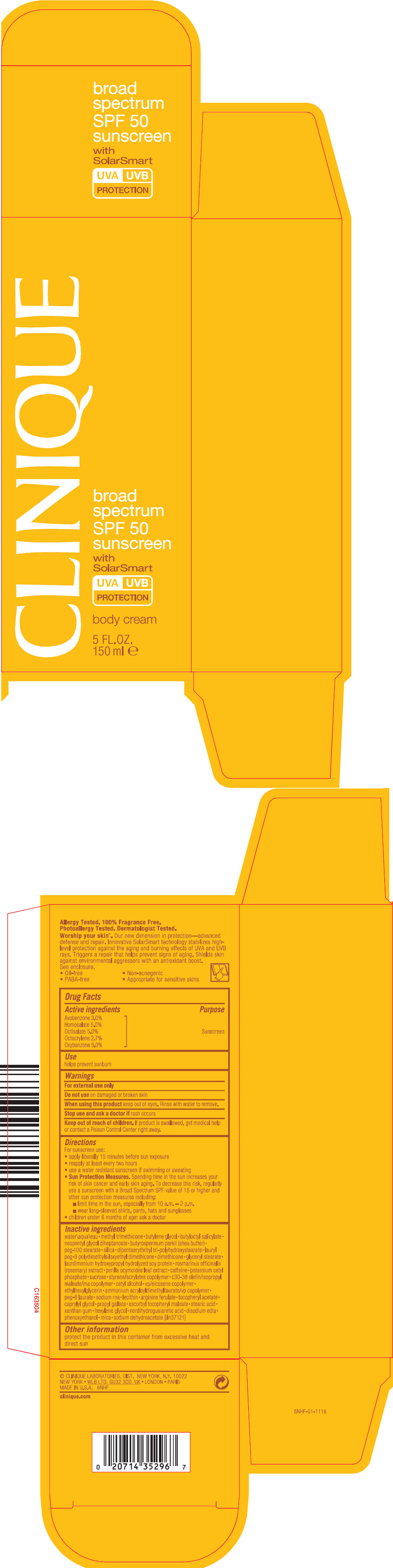 DRUG LABEL: CLINIQUE  BROAD SPECTRUM SPF 50 SUNSCREEN BODY WITH SOLAR SMART
NDC: 49527-069 | Form: CREAM
Manufacturer: CLINIQUE LABORATORIES LLC
Category: otc | Type: HUMAN OTC DRUG LABEL
Date: 20231013

ACTIVE INGREDIENTS: AVOBENZONE 30 mg/1 mL; HOMOSALATE 50 mg/1 mL; OCTISALATE 50 mg/1 mL; OCTOCRYLENE 27 mg/1 mL; OXYBENZONE 50 mg/1 mL
INACTIVE INGREDIENTS: ASCORBYL TOCOPHERYL MALEATE; STEARIC ACID; XANTHAN GUM; HEXYLENE GLYCOL; EDETATE DISODIUM ANHYDROUS; PHENOXYETHANOL; MICA; SODIUM DEHYDROACETATE; WATER; METHYL TRIMETHICONE; BUTYLENE GLYCOL; BUTYLOCTYL SALICYLATE; NEOPENTYL GLYCOL DIHEPTANOATE; SHEA BUTTER; PEG-100 STEARATE; SILICON DIOXIDE; DIPENTAERYTHRITYL TRI-POLYHYDROXYSTEARATE; LAURYL PEG-9 POLYDIMETHYLSILOXYETHYL DIMETHICONE; DIMETHICONE; GLYCERYL MONOSTEARATE; ROSEMARY; CAFFEINE; POTASSIUM CETYL PHOSPHATE; SUCROSE; CETYL ALCOHOL; ETHYLHEXYLGLYCERIN; AMMONIUM ACRYLOYLDIMETHYLTAURATE/VP COPOLYMER; PEG-8 LAURATE; ARGININE FERULATE; CAPRYLYL GLYCOL; PROPYL GALLATE

CLINIQUE BROAD SPECTRUM SPF 50 SUNSCREEN BODY CREAM WITH SOLAR SMART

Drug Facts

Active ingredients

Avobenzone 3.0%
Homosalate 5.0%
Octisalate 5.0%
Octocrylene 2.7%
Oxybenzone 5.0%

Purpose

Sunscreen

Use

helps prevent sunburn

Warnings

For external use only

Do not use on damaged or broken skin

When using this product keep out of eyes. Rinse with water to remove.

Stop use and ask a doctor if rash occurs

Keep out of reach of children. If product is swallowed, get medical help or contact a Poison Control Center right away.

Directions

For sunscreen use:

- apply liberally 15 minutes before sun exposure
- reapply at least every two hours
- use a water resistant sunscreen if swimming or sweating
- Sun Protection Measures. Spending time in the sun increases your risk of skin cancer and early skin aging. To decrease this risk, regularly use a sunscreen with a Broad Spectrum SPF value of 15 or higher and other sun protection measures including:
  - limit time in the sun, especially from 10 a.m. – 2 p.m.
  - wear long-sleeved shirts, pants, hats and sunglasses
- children under 6 months of age: ask a doctor

Inactive ingredients

water\aqua\eau • methyl trimethicone • butylene glycol • butyloctyl salicylate • neopentyl glycol diheptanoate • butyrospermum parkii (shea butter) • peg-100 stearate • silica • dipentaerythrityl tri-polyhydroxystearate • lauryl peg-9 polydimethylsiloxyethyl dimethicone • dimethicone • glyceryl stearate • laurdimonium hydroxypropyl hydrolyzed soy protein • rosmarinus officinalis (rosemary) extract • perilla ocymoides leaf extract • caffeine • potassium cetyl phosphate • sucrose • styrene/acrylates copolymer • c30-38 olefin/isopropyl maleate/ma copolymer • cetyl alcohol • vp/eicosene copolymer • ethylhexylglycerin • ammonium acryloyldimethyltaurate/vp copolymer • peg-8 laurate • sodium rna • lecithin • arginine ferulate • tocopheryl acetate • caprylyl glycol • propyl gallate • ascorbyl tocopheryl maleate • stearic acid • xanthan gum • hexylene glycol • nordihydroguaiaretic acid • disodium edta • phenoxyethanol • mica • sodium dehydroacetate [iln37121]

Other information

protect the product in this container from excessive heat and direct sun

PRINCIPAL DISPLAY PANEL - 150 ml Tube Carton

CLINIQUE

broad
spectrum
SPF 50
sunscreen
with
SolarSmart

UVA UVB
PROTECTION

body cream

5 FL. OZ.
150 ml e